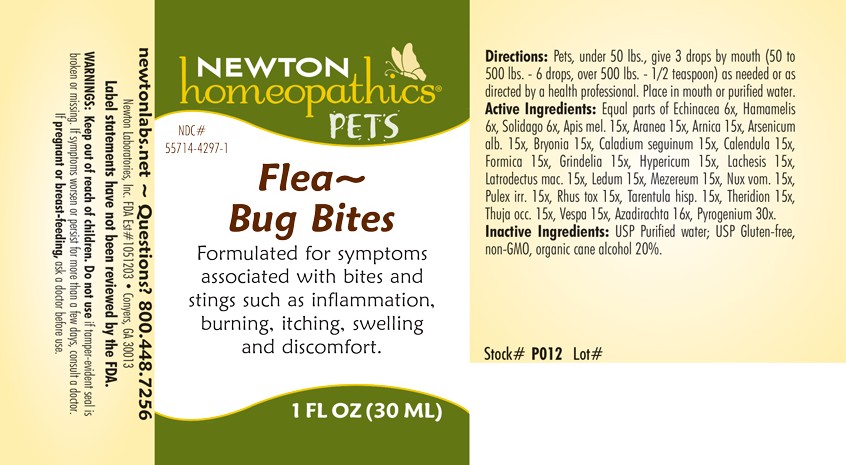 DRUG LABEL: Flea - Bug Bites
NDC: 55714-4297 | Form: LIQUID
Manufacturer: Newton Laboratories, Inc.
Category: homeopathic | Type: OTC ANIMAL DRUG LABEL
Date: 20250806

ACTIVE INGREDIENTS: Rancid Beef 30 [hp_X]/1 mL; Apis Mellifera 15 [hp_X]/1 mL; Araneus Diadematus 15 [hp_X]/1 mL; Arnica Montana 15 [hp_X]/1 mL; Arsenic Trioxide 15 [hp_X]/1 mL; Azadirachta Indica Bark 16 [hp_X]/1 mL; Bryonia Alba Root 15 [hp_X]/1 mL; Dieffenbachia Seguine 15 [hp_X]/1 mL; Calendula Officinalis Flowering Top 15 [hp_X]/1 mL; Formica Rufa 15 [hp_X]/1 mL; Grindelia Hirsutula Flowering Top 15 [hp_X]/1 mL; Hypericum Perforatum 15 [hp_X]/1 mL; Lachesis Muta Venom 15 [hp_X]/1 mL; Latrodectus Mactans 15 [hp_X]/1 mL; Ledum Palustre Twig 15 [hp_X]/1 mL; Daphne Mezereum Bark 15 [hp_X]/1 mL; Strychnos Nux-vomica Seed 15 [hp_X]/1 mL; Pulex Irritans 15 [hp_X]/1 mL; Toxicodendron Pubescens Leaf 15 [hp_X]/1 mL; Lycosa Tarantula 15 [hp_X]/1 mL; Theridion Curassavicum 15 [hp_X]/1 mL; Cedar Leaf Oil 15 [hp_X]/1 mL; Vespa Crabro 15 [hp_X]/1 mL; Echinacea, Unspecified 6 [hp_X]/1 mL; Hamamelis Virginiana Root Bark/stem Bark 6 [hp_X]/1 mL; Solidago Virgaurea Flowering Top 6 [hp_X]/1 mL
INACTIVE INGREDIENTS: Alcohol; Water

Flea - Bug Bites

INDICATIONS & USAGE SECTION

Formulated for symptoms associated with bites and stings such as inflammation, burning, itching, swelling and discomfort.

DOSAGE & ADMINISTRATION SECTION

Directions: Pets, under 50 lbs., give 3 drops by mouth (50 to 500 lbs. - 6 drops, over 500 lbs. - 1/2 teaspoon) as needed or as directed by a health professional. Place in mouth or purified water.

OTC - ACTIVE INGREDIENT SECTION

Equal parts of Echinacea 6x, Hamamelis 6x, Solidago 6x, Apis mel. 15x, Aranea 15x, Arnica 15x, Arsenicum alb. 15x, Bryonia 15x, Caladium seguinum 15x, Calendula 15x, Formica 15x, Grindelia 15x, Hypericum 15x, Lachesis 15x, Latrodectus mac. 15x, Ledum 15x, Mezereum 15x, Nux vom. 15x, Pulex irr. 15x, Rhus tox. 15x, Tarentula hisp. 15x, Theridion 15x, Thuja occ. 15x, Vespa 15x, Azadirachta 16x, Pyrogenium 30x.

OTC - PURPOSE SECTION

Formulated for symptoms associated with bites and stings such as inflammation, burning, itching, swelling and discomfort.

INACTIVE INGREDIENT SECTION

Inactive Ingredients: USP Purified Water; USP Gluten-free, non-GMO, organic cane alcohol 20%.

QUESTIONS SECTION

newtonlabs.net Questions? 1.800.448.7256
Newton Laboratories, Inc. FDA Est # 1051203 - Conyers, GA 30013

WARNINGS SECTION

WARNINGS: Keep out of reach of children. Do not use if tamper-evident seal is broken or missing. If symptoms worsen or persist for more than a few days, consult a doctor. If pregnant or breast-feeding, ask a doctor before use.

OTC - PREGNANCY OR BREAST FEEDING SECTION

If pregnant or breast-feeding, ask a doctor before use.

OTC - KEEP OUT OF REACH OF CHILDREN SECTION

Keep out of reach of children.